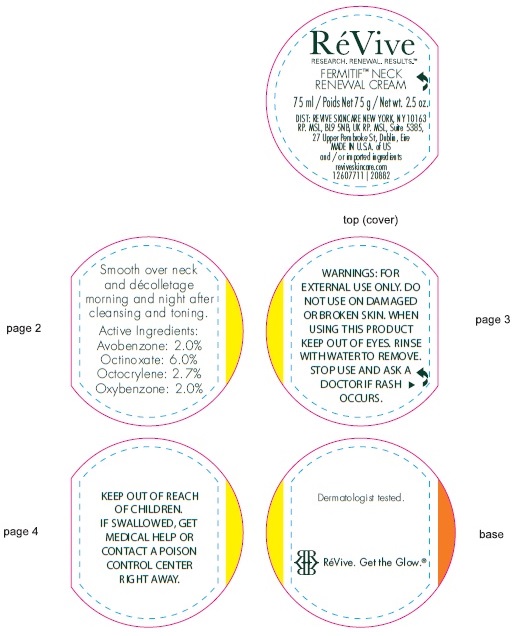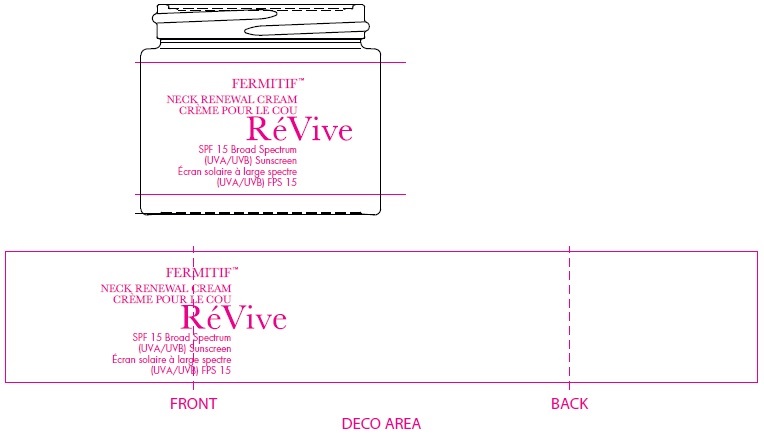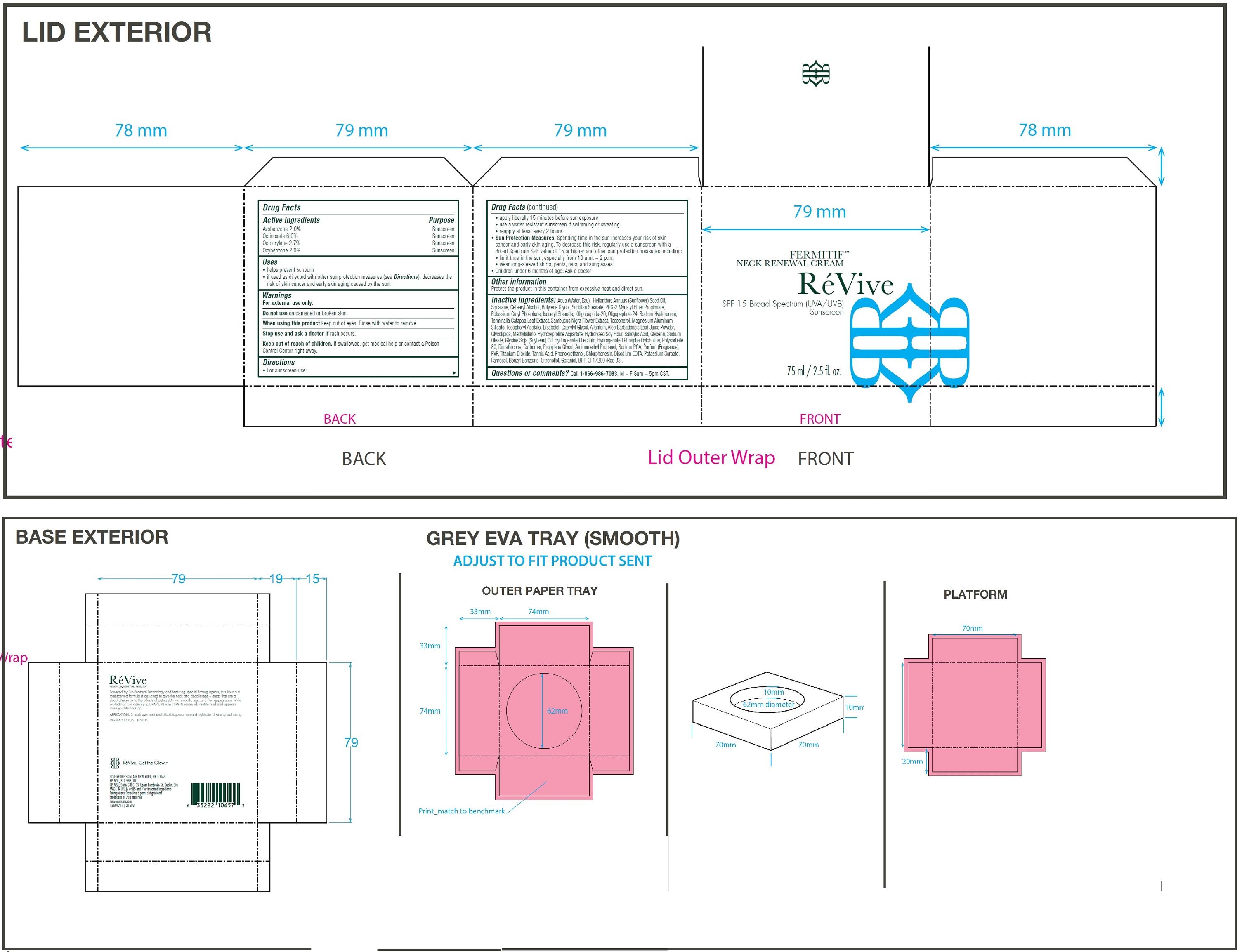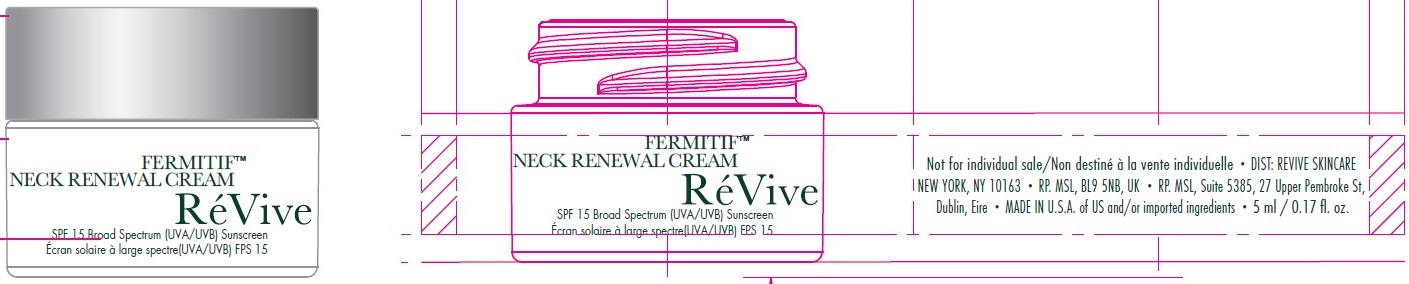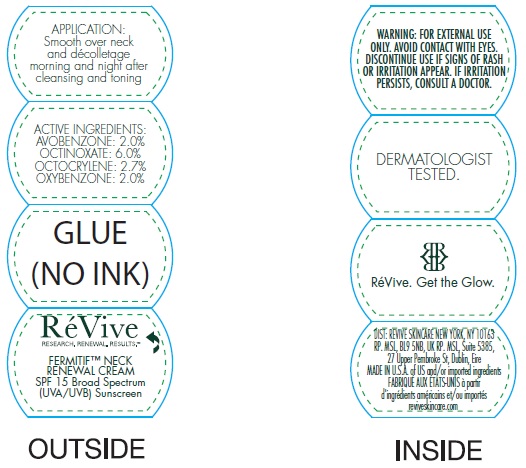 DRUG LABEL: Fermitif Neck Renewal Cream Broad Spectrum SPF 15 Sunscreen US
NDC: 82691-141 | Form: CREAM
Manufacturer: RV Skincare LLC
Category: otc | Type: HUMAN OTC DRUG LABEL
Date: 20231106

ACTIVE INGREDIENTS: AVOBENZONE 20 mg/1 mL; OCTINOXATE 60 mg/1 mL; OCTOCRYLENE 27 mg/1 mL; OXYBENZONE 20 mg/1 mL
INACTIVE INGREDIENTS: WATER; SUNFLOWER OIL; SQUALANE; CETOSTEARYL ALCOHOL; BUTYLENE GLYCOL; SORBITAN MONOSTEARATE; PPG-2 MYRISTYL ETHER PROPIONATE; POTASSIUM CETYL PHOSPHATE; ISOCETYL STEARATE; HYALURONATE SODIUM; TERMINALIA CATAPPA LEAF; SAMBUCUS NIGRA FLOWER; TOCOPHEROL; MAGNESIUM ALUMINUM SILICATE; .ALPHA.-TOCOPHEROL ACETATE; LEVOMENOL; CAPRYLYL GLYCOL; ALLANTOIN; ALOE VERA LEAF; SALICYLIC ACID; GLYCERIN; SODIUM OLEATE; SOYBEAN OIL; POLYSORBATE 80; DIMETHICONE; CARBOMER HOMOPOLYMER, UNSPECIFIED TYPE; PROPYLENE GLYCOL; AMINOMETHYLPROPANOL; SODIUM PYRROLIDONE CARBOXYLATE; POVIDONE, UNSPECIFIED; TITANIUM DIOXIDE; TANNIC ACID; PHENOXYETHANOL; CHLORPHENESIN; EDETATE DISODIUM ANHYDROUS; POTASSIUM SORBATE; FARNESOL; BENZYL BENZOATE; .BETA.-CITRONELLOL, (R)-; GERANIOL; BUTYLATED HYDROXYTOLUENE; D&C RED NO. 33

Fermitif Neck Renewal Cream Broad Spectrum SPF 15 Sunscreen US

Active ingredients

Avobenzone 2.0%

Octinoxate 6.0%

Octocrylene 2.7%

Oxybenzone 2.0%

Purpose

Sunscreen

Uses

• helps prevent sunburn

• if used as directed with other sun protection measures (see Directions), decreases the risk of skin cancer and early skin aging caused by the sun.

Warnings

For external use only.

Do not use

on damaged or broken skin.

When using this product

keep out of eyes. Rinse with water to remove.

Stop use and ask a doctor if

rash occurs.

Keep out of reach of children.

If swallowed, get medical help or contact a Poison Control Center right away.

Directions

• For sunscreen use: • apply liberally 15 minutes before sun exposure • use a water resistant sunscreen if swimming or sweating • reapply at least every 2 hours • Spending time in the sun increases your risk of skin cancer and early skin aging. To decrease this risk, regularly use a sunscreen with a Broad Spectrum SPF value of 15 or higher and other sun protection measures including: • limit time in the sun, especially from 10 a.m. – 2 p.m. • wear long-sleeved shirts, pants, hats, and sunglasses • Children under 6 months of age: Ask a doctor
Sun Protection Measures.

Other information

Protect the product in this container from excessive heat and direct sun.

Inactive ingredients:

Aqua (Water, Eau), Helianthus Annuus (Sunflower) Seed Oil, Squalane, Cetearyl Alcohol, Butylene Glycol, Sorbitan Stearate, PPG-2 Myristyl Ether Propionate, Potassium Cetyl Phosphate, Isocetyl Stearate, Oligopeptide-20, Oligopeptide-24, Sodium Hyaluronate, Terminalia Catappa Leaf Extract, Sambucus Nigra Flower Extract, Tocopherol, Magnesium Aluminum Silicate, Tocopheryl Acetate, Bisabolol, Caprylyl Glycol, Allantoin, Aloe Barbadensis Leaf Juice Powder, Glycolipids, Methylsilanol Hydroxyproline Aspartate, Hydrolyzed Soy Flour, Salicylic Acid, Glycerin, Sodium Oleate, Glycine Soja (Soybean) Oil, Hydrogenated Lecithin, Hydrogenated Phosphatidylcholine, Polysorbate 80, Dimethicone, Carbomer, Propylene Glycol, Aminomethyl Propanol, Sodium PCA, Parfum (Fragrance), PVP, Titanium Dioxide. Tannic Acid, Phenoxyethanol, Chlorphenesin, Disodium EDTA, Potassium Sorbate, Farnesol, Benzyl Benzoate, Citronellol, Geraniol, BHT, CI 17200 (Red 33).

Questions or comments?

Call , M – F 8am – 5pm CST. 1-866-986-7083